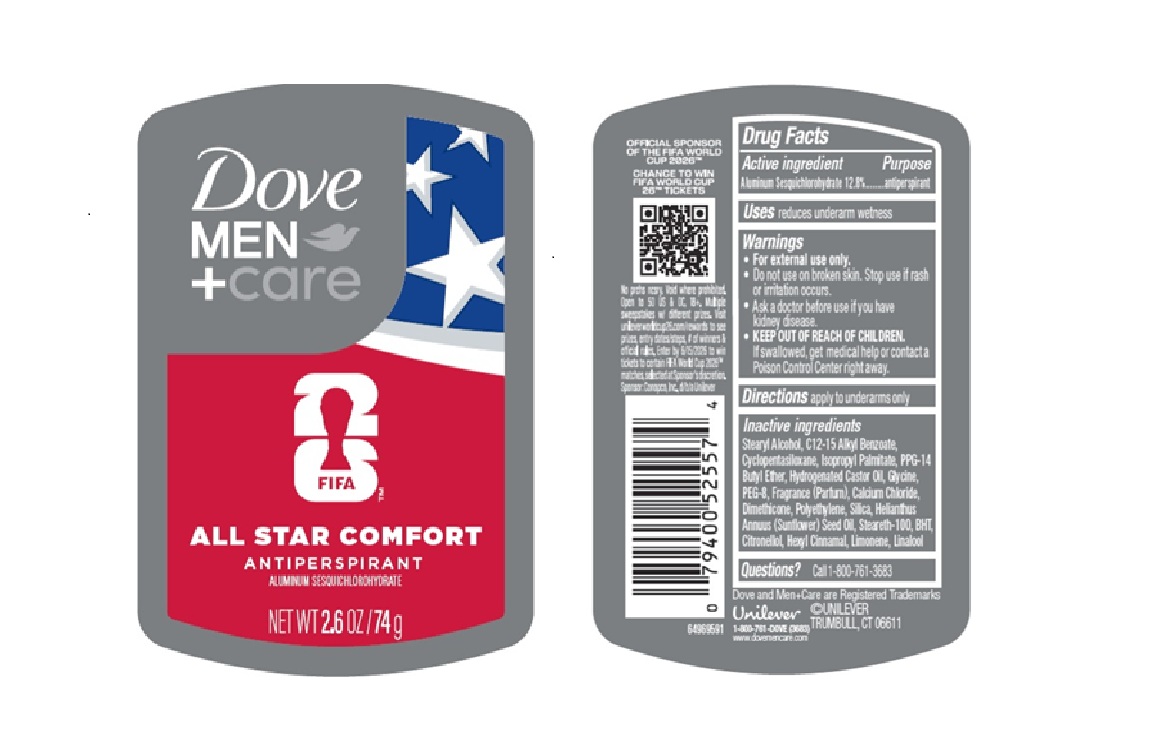 DRUG LABEL: Dove Men Care
NDC: 64942-2410 | Form: STICK
Manufacturer: Conopco d/b/a Unilever
Category: otc | Type: HUMAN OTC DRUG LABEL
Date: 20251204

ACTIVE INGREDIENTS: ALUMINUM SESQUICHLOROHYDRATE 12.8 g/100 g
INACTIVE INGREDIENTS: CALCIUM CHLORIDE; PEG-8; CITRONELLOL; HYDROGENATED CASTOR OIL; DIMETHICONE; SILICA; BHT; POLYETHYLENE; HELIANTHUS ANNUUS (SUNFLOWER) SEED OIL; C12-15 ALKYL BENZOATE; HEXYL CINNAMAL; CYCLOPENTASILOXANE; STEARYL ALCOHOL; STEARETH-100; ISOPROPYL PALMITATE; PPG-14 BUTYL ETHER; LINALOOL; GLYCINE; LIMONENE, (+)-

Dove Men + Care Fifa All Star Comfort Antiperspirant Stick

DESCRIPTION

Dove Men + Care Fifa All Star Comfort Antiperspirant Stick

ACTIVE INGREDIENT

Aluminum Sesquichlorohydrate 12.8%

PURPOSE

Antiperspirant

INDICATIONS AND USAGE

reduces underarm wetness

WARNINGS

• For external use only.
•Do not use on broken skin. Stop use if rash
or irritation occurs.
•Ask a doctor before use if you have
kidney disease.
•If swallowed, get medical help or contact a Poison Control Center right away.

• KEEP OUT OF REACH OF CHILDREN.

DOSAGE AND ADMINISTRATION

apply to underarms only

INACTIVE INGREDIENT

Stearyl Alcohol, C12-15 Alkyl Benzoate,
Cyclopentasiloxane, Isopropyl Palmitate, PPG-14
Butyl Ether, Hydrogenated Castor Oil, Glycine,
PEG-8, Fragrance (Parfum), Calcium Chloride,
Dimethicone, Polyethylene, Silica, Helianthus
Annuus (Sunflower) Seed Oil, Steareth-100, BHT,
Citronellol, Hexyl Cinnamal, Limonene, Linalool

QUESTIONS

Call 1-800-761-3683